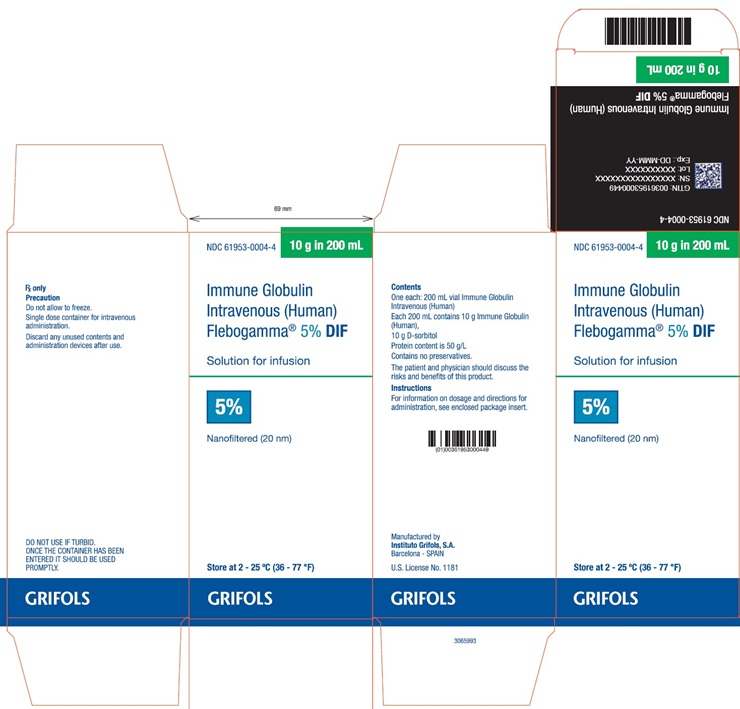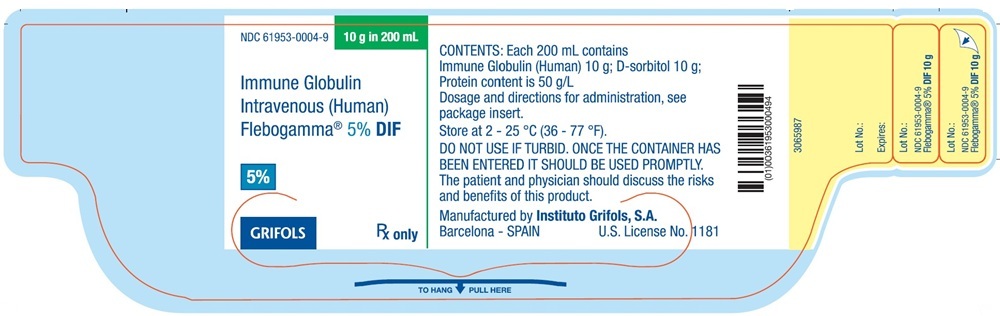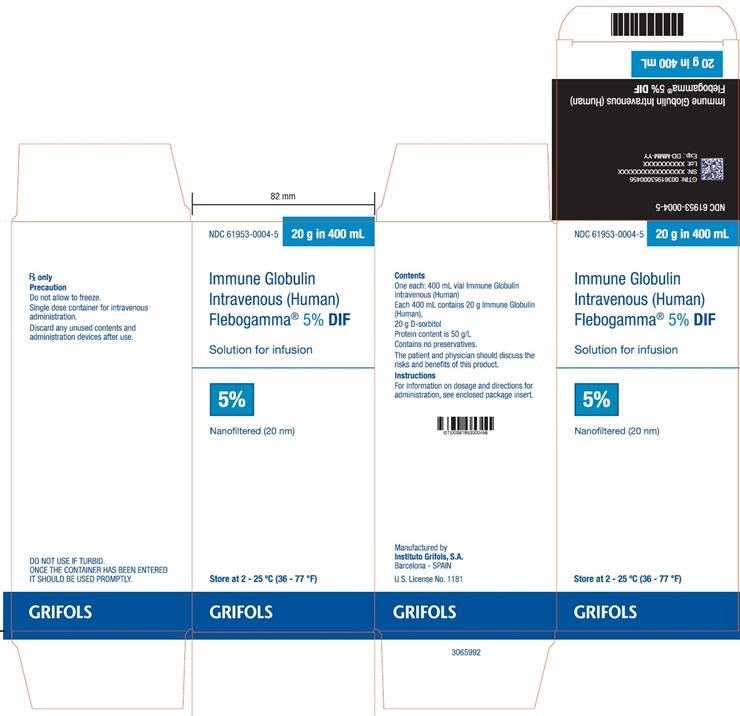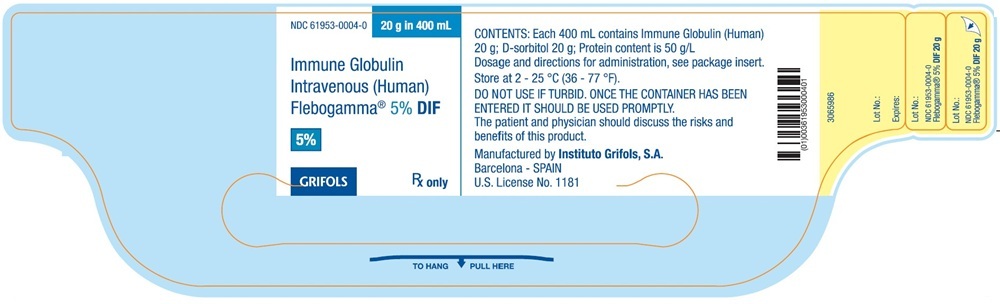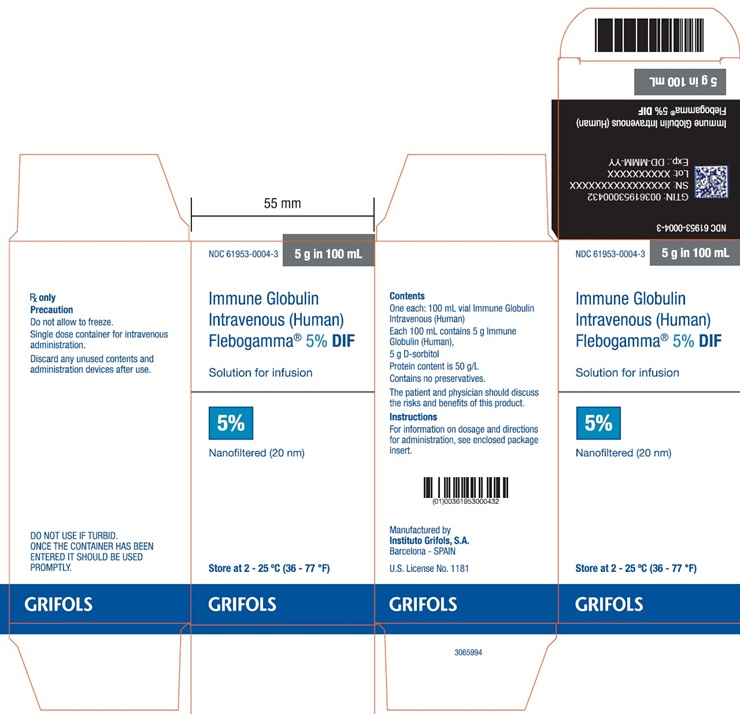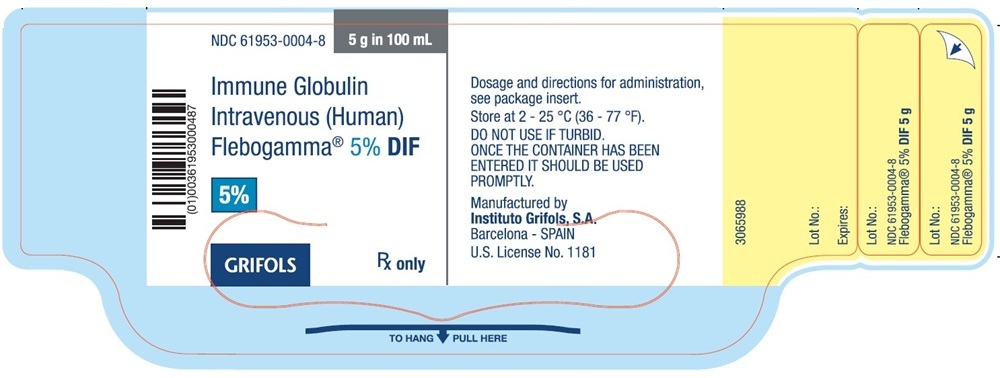 DRUG LABEL: Flebogamma
NDC: 61953-0004 | Form: INJECTION, SOLUTION
Manufacturer: GRIFOLS USA, LLC
Category: other | Type: PLASMA DERIVATIVE
Date: 20251117

ACTIVE INGREDIENTS: HUMAN IMMUNOGLOBULIN G 0.05 g/1 mL
INACTIVE INGREDIENTS: SORBITOL; WATER

HIGHLIGHTS OF PRESCRIBING INFORMATION

These highlights do not include all the information needed to use
FLEBOGAMMA 5% DIF safely and effectively.
See full prescribing information for FLEBOGAMMA 5% DIF.
FLEBOGAMMA 5% DIF (immune globulin intravenous [human]), solution
for intravenous administration
Initial U.S. Approval: 2006

RECENT MAJOR CHANGES

Dosage and Administration (2) | 9/2019

WARNING: THROMBOSIS, RENAL DYSFUNCTION, and ACUTE RENAL FAILURE

See full prescribing information for complete boxed warning.

- Thrombosis may occur with immune globulin products, including FLEBOGAMMA 5% DIF. Risk factors may include: advanced age, prolonged immobilization, hypercoagulable conditions, history of venous or arterial thrombosis, use of estrogens, indwelling vascular catheters, hyperviscosity, and cardiovascular risk factors.
- For patients at risk of thrombosis administer FLEBOGAMMA 5% DIF at the minimum dose and infusion rate practicable. Ensure adequate hydration in patients before administration. Monitor for signs and symptoms of thrombosis and assess blood viscosity in patients at risk of hyperviscosity.
- Renal dysfunction, acute renal failure, osmotic nephrosis and death may occur with the administration of human immune globulin intravenous (IGIV) products, particularly those products that contain sucrose. FLEBOGAMMA 5% DIF does not contain sucrose.
- For patients at risk of renal dysfunction or failure, administer FLEBOGAMMA 5% DIF at the minimum dose and infusion rate practicable. (5.2)

1 INDICATIONS AND USAGE

Flebogamma 5% DIF is an immune globulin intravenous (human), indicated for treatment of primary (inherited) immunodeficiency (PI) in adults and pediatric patients 2 years of age and older. (1)

2 DOSAGE AND ADMINISTRATION

For Intravenous Use Only

Indication | Dose | Initial Infusion Rate | Maintenance Dose Rate (if tolerated)
PI | 300-600 mg per kg every 3-4 weeks | 0.01 mL per kg per minute (0.5 mg per kg per min) | Increase to 0.10 mL per kg per minute (5 mg per kg per min)

- For patients at risk of renal dysfunction or thrombosis, administer Flebogamma 5% DIF at the minimum dose and infusion rate practicable. (5.2, 5.4)
- Ensure that patients with pre-existing renal insufficiency are not volume-depleted and discontinue Flebogamma 5% DIF if renal function deteriorates. (5.2)

3 DOSAGE FORMS AND STRENGTHS

Solution for intravenous injection containing 5% IgG (50 mg per mL). (3)

4 CONTRAINDICATIONS

- History of anaphylactic or severe systemic reactions to human immunoglobulin. (4)
- IgA-deficient patients with antibodies against IgA and a history of hypersensitivity. (4)

5 WARNINGS AND PRECAUTIONS

- IgA-deficient patients with antibodies to IgA are at greater risk of developing severe hypersensitivity and anaphylactic reactions. (5.1)
- Monitor renal function, including blood urea nitrogen, serum creatinine, and urine output in patients at risk of developing acute renal failure. (5.2)
- Hyperproteinemia, increased serum viscosity, and hyponatremia may occur in patients receiving Flebogamma 5% DIF therapy. (5.3)
- Thrombosis may occur. Monitor patients with known risk factors for thrombosis and consider baseline assessment of blood viscosity for those at risk of hyperviscosity. (5.4)
- Aseptic meningitis syndrome (AMS) may occur in patients receiving Flebogamma 5% DIF therapy, especially with high doses or rapid infusion. (5.5)
- Hemolysis, either intravascular or due to enhanced red blood cell sequestration, can develop subsequent to Flebogamma 5% DIF treatments. Risk factors include high doses and non-O blood group. Monitor patients for hemolysis and hemolytic anemia. (5.6)
- Monitor patients for pulmonary adverse reactions (transfusion-related acute lung injury, TRALI). (5.7)
- Patients receiving Flebogamma 5% DIF for the first time or being restarted on the product after a treatment hiatus of more than 8 weeks may be at a higher risk for development of fever, chills, nausea, and vomiting. (5.8)
- Flebogamma 5% DIF is made from human plasma and may contain infectious agents, e.g., viruses, the variant Creutzfeldt-Jakob disease (vCJD) agent and, theoretically, the Creutzfeldt-Jakob disease (CJD) agent. (5.9)
- Passive transfer of antibodies may confound serologic testing. (5.11)
- Flebogamma 5% DIF contains sorbitol. The presence of sorbitol presents a risk to those with hereditary fructose intolerance (HFI). (5.12)

6 ADVERSE REACTIONS

The most common adverse reactions (reported in at least 5% of clinical trial adult subjects) were headache, pyrexia/fever, pain, infusion site reactions, diarrhea, rigors or chills, urticaria, and infusion site inflammation. (6)

The most common adverse reactions (reported in at least 5% of clinical trial pediatric subjects) were headache, pyrexia, hypotension, tachycardia, diastolic hypotension, nausea, abdominal pain, diarrhea, pain, and vomiting. (6)

To report SUSPECTED ADVERSE REACTIONS, contact Grifols Biologicals at 1-888-GRIFOLS (1-888-474-3657) or FDA at 1-800-FDA-1088 or www.fda.gov/medwatch.

7 DRUG INTERACTIONS

Passive transfer of antibodies may transiently interfere with the immune response to live virus vaccines, such as measles, mumps, and rubella. (7)

8 USE IN SPECIFIC POPULATIONS

- Pregnancy: No human or animal data. Use only if clearly needed. (8.1)
- Geriatric: In patients over age 65 or in any patient at risk of developing renal insufficiency, do not exceed the recommended dose, and infuse Flebogamma 5% DIF at the minimum dose and infusion rate practicable and at less than 0.06 mL per kg per minute (3 mg per kg per min). (8.5)

FULL PRESCRIBING INFORMATION

WARNING: THROMBOSIS, RENAL DYSFUNCTION, and ACUTE RENAL FAILURE

- Thrombosis may occur with immune globulin products, including FLEBOGAMMA 5% DIF. Risk factors may include: advanced age, prolonged immobilization, hypercoagulable conditions, history of venous or arterial thrombosis, use of estrogens, indwelling central vascular catheters, hyperviscosity, and cardiovascular risk factors. Thrombosis may occur in the absence of known risk factors. (see Warnings and Precautions [5.4] and Patient Counseling Information [17])
- For patients at risk of thrombosis, administer FLEBOGAMMA 5% DIF at the minimum dose and infusion rate practicable. Ensure adequate hydration in patients before administration. Monitor for signs and symptoms of thrombosis and assess blood viscosity in patients at risk for hyperviscosity. (see Dosage and Administration [2.3] and Warnings and Precautions [5.4])
- Renal dysfunction, acute renal failure, osmotic nephrosis, and death^1 have been related to intravenous immune globulin (IGIV) products. Patients predisposed to acute renal failure include patients with any degree of pre-existing renal insufficiency, diabetes mellitus, age greater than 65, volume depletion, sepsis, paraproteinemia, or patients receiving known nephrotoxic drugs.
- Administer FLEBOGAMMA 5% DIF at the minimum dose and rate of infusion practicable in patients at risk for renal dysfunction or failure.
- Reports of renal dysfunction and acute renal failure occur more commonly in patients receiving IGIV products containing sucrose as a stabilizer. They account for a disproportionate share of the total number of reported cases of renal dysfunction and acute renal failure. FLEBOGAMMA 5% DIF does not contain sucrose. (see Dosage and Administration [2.3] and Warnings and Precautions [5.2])

1 INDICATIONS AND USAGE

Flebogamma 5% DIF is an immune globulin intravenous (human) solution indicated in adults and pediatric patients 2 years of age and older for the treatment of primary immunodeficiency (PI), including the humoral immune defects in common variable immunodeficiency, x-linked agammaglobulinemia, severe combined immunodeficiency, and Wiskott-Aldrich syndrome.

2 DOSAGE AND ADMINISTRATION

For Intravenous Use Only

2.1 Dosage

Treatment of Primary Immunodeficiency (PI)

Dose | Initial Infusion Rate | Maintenance Dose Rate (if tolerated)
300-600 mg per kg body weight (6.0-12.0 mL per kg) administered every 3-4 weeks | 0.01 mL per kg per minute (0.5 mg per kg per min) | Increase to 0.10 mL per kg per minute (5 mg per kg per min)

If a patient has been exposed to measles, it may be prudent to administer an extra dose of IGIV as soon as possible and within 6 days of exposure. A dose of 400 mg/kg should provide a serum level > 240 mIU/mL of measles antibodies for at least two weeks.

If a patient is at risk of future measles exposure and receives a dose of less than 530 mg/kg every 3-4 weeks, the dose should be increased to at least 530 mg/kg. This should provide a serum level of 240 mIU/mL of measles antibodies for at least 22 days after infusion.

As there are significant differences in the half-life of IgG among patients with PI, the frequency and amount of immunoglobulin therapy may vary from patient to patient. Adjust the dose according to the clinical response.

Adjust the dosage over time to achieve the desired trough IgG levels and clinical responses. No randomized controlled trial data are available to determine an optimum target trough serum IgG level.

2.2 Preparation and Handling

- Inspect Flebogamma 5% DIF visually for particulate matter and color prior to administration. Do not use the vial if particles are detected. Do not use if turbid.
- Several vials of Flebogamma 5% DIF may be pooled into an empty sterile solution container by using aseptic technique, if large doses are to be administered.
- Do not dilute with intravenous fluids. Do not inject other medications into intravenous tubing being used for Flebogamma 5% DIF.
- Infuse Flebogamma 5% DIF through a separate intravenous line. Do not add any medications or intravenous fluids to the Flebogamma 5% DIF infusion container. Do not mix IGIV products of different formulations or from different manufacturers.
- Discard unused contents and administration devices after use.
- Use promptly any vial that has been entered.
- Discard partially used vials. Do not save for future use because the solution contains no preservative.
- Do not use solution that has been frozen.

2.3 Administration

The recommended initial infusion rate of Flebogamma 5% DIF is 0.01 mL per kg body weight per minute (0.5 mg per kg per min). If the infusion is well-tolerated during the first 30 minutes, the rate may be gradually increased to a maximum of 0.10 mL per kg per minute (5 mg per kg per min).

Monitor patient vital signs throughout the infusion. Slow or stop infusion if adverse reactions occur. If symptoms subside promptly, the infusion may be resumed at a lower rate that is comfortable for the patient.

3 DOSAGE FORMS AND STRENGTHS

Flebogamma 5% DIF is a liquid preparation containing 5% IgG (50 mg per mL).

4 CONTRAINDICATIONS

- Flebogamma 5% DIF is contraindicated in patients who have had a history of anaphylactic or severe systemic hypersensitivity reactions to the administration of human immune globulin.
- Flebogamma 5% DIF is contraindicated in IgA-deficient patients with antibodies to IgA and a history of hypersensitivity. (see Warnings and Precautions [5.1])

5 WARNINGS AND PRECAUTIONS

5.1 Hypersensitivity

Severe hypersensitivity reactions and anaphylactic reactions with a fall in blood pressure may occur, even in patients who had tolerated previous treatment with IGIV. (see Contraindications [4]) If hypersensitivity reaction develops, discontinue Flebogamma 5% DIF infusion immediately and institute appropriate treatment.

Flebogamma 5% DIF contains trace amounts of IgA (less than 50 μg/mL). (see Description [11]) Patients with antibodies to IgA have a greater risk of developing potentially severe hypersensitivity and anaphylactic reactions. Flebogamma 5% DIF is contraindicated in patients with antibodies against IgA and a history of hypersensitivity reaction. (see Contraindications [4])

5.2 Renal Dysfunction/Failure

Acute renal dysfunction/failure, acute tubular necrosis, proximal tubular nephropathy, osmotic nephrosis, and death have been reported in patients receiving IGIV, particularly those products containing sucrose^2. Flebogamma 5% DIF does not contain sucrose.

Ensure that patients are not volume-depleted before administering Flebogamma 5% DIF. For patients judged to be at risk for developing renal dysfunction, including patients with any degree of pre-existing renal insufficiency, diabetes mellitus, age greater than 65, volume depletion, sepsis, paraproteinemia, or patients receiving known nephrotoxic drugs, administer Flebogamma 5% DIF at the minimum dose and rate of infusion practicable^3. (see Boxed Warning, Dosing and Administration [2.3])

Periodic monitoring of renal function and urine output is particularly important in patients judged to be at increased risk of developing acute renal failure^1. Assess renal function, including measurement of blood urea nitrogen (BUN) and serum creatinine, before the initial infusion of Flebogamma 5% DIF and at appropriate intervals thereafter. If renal function deteriorates, consider discontinuation of the product.

5.3 Hyperproteinemia, Increased Serum Viscosity, and Hyponatremia

Hyperproteinemia, increased serum viscosity, and hyponatremia may occur in patients receiving Flebogamma 5% DIF therapy. It is clinically critical to distinguish true hyponatremia from a pseudohyponatremia that is temporally or causally related to hyperproteinemia with concomitant decreased calculated serum osmolarity or elevated osmolar gap, because treatment aimed at decreasing serum free water in patients with pseudohyponatremia may lead to volume depletion, a further increase in serum viscosity, and a higher risk of thrombosis.

5.4 Thrombosis

Thrombosis may occur following treatment with immune globulin products, including Flebogamma 5% DIF. Risk factors may include advanced age, prolonged immobilization, hypercoagulable conditions, history of venous or arterial thrombosis, use of estrogens, indwelling central vascular catheters, hyperviscosity, and cardiovascular risk factors. Thrombosis may occur in the absence of known risk factors.

Consider baseline assessment of blood viscosity in patients at risk for hyperviscosity, including those with cryoglobulins, fasting chylomicronemia/markedly high triacylglycerols (triglycerides), or monoclonal gammopathies. (see Warnings and Precautions [5.10]) For patients at risk of thrombosis, administer Flebogamma 5% DIF at the minimum dose and infusion rate practicable. Ensure adequate hydration in patients before administration. Monitor for signs and symptoms of thrombosis and assess blood viscosity in patients at risk for hyperviscosity. (see Boxed Warning, Dosage and Administration [2.3], and Patient Counseling Information [17])

5.5 Aseptic Meningitis Syndrome (AMS)

AMS has been reported to occur following IGIV treatment. Discontinuation of IGIV treatment has resulted in remission of AMS within several days without sequelae^4-7. The symptoms of AMS usually begin within several hours to 2 days following IGIV treatment.

AMS is characterized by the following signs and symptoms: severe headache, nuchal rigidity, drowsiness, fever, photophobia, painful eye movements, nausea, and vomiting. (see Patient Counseling Information [17]) Cerebrospinal fluid (CSF) studies frequently reveal pleocytosis up to several thousand cells per cubic millimeter, predominantly from the granulocytic series, and elevated protein levels up to several hundred mg/dL, but negative culture results. Conduct a thorough neurological examination to patients exhibiting such signs and symptoms, including CSF studies, to rule out other causes of meningitis.

AMS may occur more frequently following high-dose (e.g. over 1.0 g per kg body weight) or rapid infusion of IGIV.

5.6 Hemolysis

Flebogamma 5% DIF may contain blood group antibodies that may act as hemolysins and induce in vivo coating of red blood cells (RBCs) with immunoglobulin, causing a positive direct antiglobulin test (DAT) (Coombs' test) result and hemolysis^8-11. Delayed hemolytic anemia can develop subsequent to IGIV therapy due to enhanced RBC sequestration and acute hemolysis, consistent with intravascular hemolysis, has been reported^12. Cases of severe hemolysis-related renal dysfunction/failure or disseminated intravascular coagulation have occurred following infusion of IGIV.

The following risk factors may be associated with the development of hemolysis following IGIV administration: high doses (e.g., at least 2 g per kg), given either as a single administration or divided over several days, and non-O blood group^13. Other individual patient factors, such as an underlying inflammatory state (as may be reflected by, for example, elevated C-reactive protein or erythrocyte sedimentation rate), have been hypothesized to increase the risk of hemolysis following administration of IGIV^14, but their role is uncertain. Hemolysis has been reported following administration of IGIV for a variety of indications, including ITP and PI^11. Monitor patients for clinical signs and symptoms of hemolysis, particularly patients with risk factors noted above. Consider appropriate laboratory testing in higher risk patients, including measurement of hemoglobin or hematocrit prior to infusion and within 36 to 96 hours post infusion. If clinical signs and symptoms of hemolysis or a significant drop in hemoglobin or hematocrit have been observed, perform appropriate confirmatory laboratory testing. If transfusion is indicated for patients who develop hemolysis with clinically compromising anemia after receiving IGIV, perform adequate cross-matching to avoid exacerbating on-going hemolysis. (see Patient Counseling Information [17])

5.7 Transfusion-Related Acute Lung Injury (TRALI)

Non-cardiogenic pulmonary edema has been reported in patients following IGIV treatment^15. TRALI is characterized by severe respiratory distress, pulmonary edema, hypoxemia, normal left ventricular function, and fever. Symptoms typically appear within 1 to 6 hours after transfusion.

Monitor patients for pulmonary adverse reactions. (see Patient Counseling Information [17]) If TRALI is suspected, perform appropriate tests for the presence of antineutrophil antibodies and anti-HLA antibodies in both the product and patient serum. TRALI may be managed by using oxygen therapy with adequate ventilatory support.

5.8 Infusion Reactions

Individuals receiving Flebogamma 5% DIF for the first time, or being restarted on the product after a treatment hiatus of more than 8 weeks, may be at a higher risk for the development of fever, chills, nausea, and vomiting. Careful monitoring of recipients and adherence to recommendations regarding dosage and administration may reduce the risk of these types of events. (see Dosage and Administration [2.3])

5.9 Transmissible Infectious Agents

Because Flebogamma 5% DIF is made from human plasma, it may carry a risk of transmitting infectious agents, e.g., viruses, the variant Creutzfeldt-Jakob disease (vCJD) agent and, theoretically, the Creutzfeldt-Jakob disease (CJD) agent. This also applies to unknown or emerging viruses and other pathogens. No cases of transmission of viral diseases or CJD have been associated with the use of Flebogamma 5% DIF. All infections suspected by a physician possibly to have been transmitted by this product should be reported by the physician or other healthcare provider to Grifols Biologicals at 1-888-474-3657.

Before prescribing or administering Flebogamma 5% DIF, the physician should discuss the risks and benefits of its use with the patient. (see Patient Counseling Information [17])

5.10 Monitoring: Laboratory Tests

- Periodic monitoring of renal function and urine output is particularly important in patients judged to be at increased risk of developing acute renal failure. Assess renal function, including measurement of BUN and serum creatinine, before the initial infusion of Flebogamma 5% DIF and at appropriate intervals thereafter.
- Consider baseline assessment of blood viscosity in patients at risk for hyperviscosity, including those with cryoglobulins, fasting chylomicronemia/markedly high triacylglycerols (triglycerides), or monoclonal gammopathies because of the potentially increased risk of thrombosis.
- If signs and/or symptoms of hemolysis are present after an infusion of Flebogamma 5% DIF, perform appropriate laboratory testing for confirmation.
- If TRALI is suspected, perform appropriate tests for the presence of antineutrophil antibodies and anti-HLA antibodies in both the product and patient serum.

5.11 Interference with Laboratory Tests

After infusion of IgG, the transitory rise of the various passively transferred antibodies in the patient's blood may yield positive serological testing results, with the potential for misleading interpretation. Passive transmission of antibodies to erythrocyte antigens (e.g. A, B, and D) may cause a positive direct or indirect antiglobulin (Coombs') test.

5.12 Hereditary Fructose Intolerance

Flebogamma 5% DIF contains sorbitol. The presence of sorbitol presents a risk to those with hereditary fructose intolerance (HFI). The incidence of HFI is estimated at 1 in 20,000 births and is usually diagnosed at the time of weaning when fructose or sucrose is introduced into the diet. Clinical symptoms include recurrent vomiting, abdominal pain and hypoglycemia. Flebogamma 5% DIF must not be administered to subjects with HFI.

6 ADVERSE REACTIONS

The most common adverse reactions (reported in at least 5% of clinical trial adult subjects) were headache, pyrexia/fever, pain, infusion site reactions, diarrhea, rigors or chills, urticaria, and infusion site inflammation.

The most common adverse reactions (reported in at least 5% of clinical trial pediatric subjects) were headache, pyrexia, hypotension, tachycardia, diastolic hypotension, nausea, abdominal pain, diarrhea, pain, and vomiting.

To report SUSPECTED ADVERSE REACTIONS, contact Grifols Biologicals at 1-888-GRIFOLS (1-888-474-3657) or FDA at 1-800-FDA-1088 or www.fda.gov/medwatch.

6.1 Clinical Trials Experience

Because clinical trials are conducted under widely varying conditions, adverse reaction rates observed in the clinical trials of a drug cannot be directly compared to rates in the clinical trials of another drug and may not reflect the rates observed in clinical practice.

Adverse reactions were reported in a study of 46 individuals with PI receiving infusions every 3 to 4 weeks of 300-600 mg per kg body weight. Thirty-one subjects (67.4%) had at least one adverse reaction at some time during the study that was considered product-related. None of the 46 subjects who participated in this study discontinued the study prematurely due to an adverse drug reaction.

Adverse reactions that occurred with an incidence of at least 5% on a per-subject basis are summarized in Table 1.

Table 1. Adverse Reactions Occurring in at Least 5% of Subjects
Adverse Reaction | Subjects (%) N=46 | Number of Events
Headache | 10 (21.7) | 24
Pyrexiaa | 9 (19.6) | 12
Painb | 7 (15.2) | 11
Injection site reaction | 6 (13.0) | 10
Diarrhea | 4 (8.7) | 5
Rigors | 4 (8.7) | 7
Urticaria | 3 (6.5) | 3
Infusion site inflammationc | 3 (6.6) | 3
a. include combined reported terms of pyrexia and body temperature increase.
b. include combined reported terms of pain such as pain (not otherwise specified), injection site pain, back pain, abdominal pain (not otherwise specified), and abdominal pain upper.
c. include combined reported terms of infusion site inflammation and others such as injection site oedema and injection site swelling.

Other common adverse drug reactions reported in fewer than 5% of the subjects included hypertension, sinusitis, nausea/vomiting, positive Coombs test, arthralgia, myalgia, dizziness, bronchitis, and hypotension.

The total number of adverse reactions reported whose onset were within 72 hours after the end of an infusion of Flebogamma 5% DIF was 94. There were a total of 709 infusions, resulting in a ratio of 0.13 temporally associated adverse reactions per infusion (the upper bound of the 1-sided 95% confidence interval = 0.18). Of the 709 total infusions, 70 (9.7%, 1-sided 95% upper bound CI = 12.4%) were associated with at least one adverse reaction that began within 72 hours after the completion of an infusion. In this analysis, each infusion is only counted once, regardless of the number of adverse reactions that occurred during the infusion, when during the 72-hour period after the infusion the adverse reaction started, or the intensity of those adverse reactions.

Factoring adverse reaction intensity into the analysis of the 709 infusions shows that there were 58 infusions with at least one mild adverse reaction (8.2% [upper bound 95% CI=10.5%]), 25 infusions with at least one moderate adverse reaction (3.5% [upper bound 95% CI=5.2%]), and 1 infusion with a severe adverse reaction (0.1% [upper bound 95% CI=0.8%]). In this analysis, if a subject reported multiple events with different intensities during the same infusion (e.g., mild headache and moderate pyrexia), that infusion would be counted in all relevant categories. Therefore, the number of infusions counted is 84.

Three subjects (6.5%) experienced a treatment-emergent rise in AST (> 3x the upper-limit of normal), and 1 subject (2.2%) experienced a treatment-emergent rise in ALT (> 3x the upper-limit of normal). None of these abnormal lab values were long-lasting (i.e. they occurred at 1 or 2 infusions), and none of these subjects had a concomitant treatment-emergent rise in total bilirubin.

A clinical study with Flebogamma 5% DIF for the treatment of PI was conducted in 24 pediatric subjects aged 2-16 years to determine whether they respond differently from adult subjects. Pediatric subjects received intravenous infusions of 262-625 mg per kg body weight every 3-4 weeks. Twenty subjects (83.3%) had at least one adverse reaction at some time during the study that was considered product-related. There were no deaths or serious adverse reactions.

In 317 infusions, 20 pediatric subjects reported 159 treatment-related adverse drug reactions (ADR). Treatment-related adverse reactions that occurred with an incidence of at least 5% on a per-subject basis included headache (42%), pyrexia (29%), hypotension (25%), tachycardia (25%), diastolic hypotension (21%), nausea (8%), abdominal pain (8%), diarrhea (8%), pain (8%), and vomiting (8%). Of these, 99 ADRs were mild, 54 were moderate, and 6 were severe in intensity. The most common severe ADR was headache. Tachycardia was defined as mild, moderate, or severe by ratio of heart rate over baseline of 1.2-1.4, 1.41-1.6, or >1.6, respectively. Two episodes of tachycardia were moderate and 14 were mild, 1 mild case had the infusion interrupted and the rest had no action taken, and all resolved. Hypotension was defined as mild, moderate, or severe by the decrease in pressure below baseline of 10-15%, 16-25%, and >25%, respectively. Ten episodes of hypotension/diastolic hypotension were moderate and 29 were mild, one moderate case had the infusion interrupted and the rest had no action taken, and all resolved. None of the ADRs related to fluctuation in vital signs were severe, all resolved without sequelae, and none were considered clinically significant.

One subject (6.5%) experienced a treatment-emergent rise in ALT (over 2.5x the upper-limit of normal). This was considered a mild treatment-related AE and resolved without sequelae. All other lab values were within normal limits. One subject experienced one positive Coombs' test result after baseline (experienced 14 days after the final infusion). No subjects experienced clinically significant abnormal lab values for LDH, bilirubin, serum creatinine. In addition, no subjects experienced positive test results for HBsAg, HCV, or HIV.

6.2 Post-marketing Experience

Because adverse reactions are reported voluntarily post-approval from a population of uncertain size, it is not always possible to reliably estimate their frequency or establish a causal relationship to product exposure.

The following adverse reactions have been identified during the post-approval use of IGIV products^(16, 17), including Flebogamma 5% DIF.

Infusion Reactions | Hypersensitivity (e.g. anaphylaxis), headache, diarrhea, tachycardia, fever, fatigue, dizziness, malaise, chills, flushing, urticaria or other skin reactions, wheezing or other chest discomfort, nausea, vomiting, rigors, back pain, myalgia, arthralgia, and changes in blood pressure
Renal | Acute renal dysfunction/failure, osmotic nephropathy
Respiratory | Apnea, Acute Respiratory Distress Syndrome (ARDS), Transfusion-Related Acute Lung Injury (TRALI), cyanosis, hypoxemia, pulmonary edema, dyspnea, bronchospasm
Cardiovascular | Cardiac arrest, thromboembolism, vascular collapse, hypotension
Neurological | Coma, loss of consciousness, seizures, tremor, aseptic meningitis syndrome
Integumentary | Stevens-Johnson Syndrome, epidermolysis, erythema multiformae, dermatitis (e.g. bullous dermatitis)
Hematologic | Pancytopenia, leukopenia, hemolysis, positive direct antiglobulin (Coombs) test
Musculoskeletal | Back pain
Gastrointestinal | Hepatic dysfunction, abdominal pain
General/Body as a Whole | Pyrexia, rigors

7 DRUG INTERACTIONS

Passive transfer of antibodies may transiently impair the immune response to live attenuated virus vaccines, such as measles, mumps, and rubella. Inform the immunizing physician of recent therapy with Flebogamma 5% DIF so that appropriate measures can be taken (see Patient Counseling Information [17])

8 USE IN SPECIFIC POPULATIONS

8.1 Pregnancy

Risk Summary
There are no studies of Flebogamma 5% DIF use in pregnant women. Animal reproduction studies have not been performed with Flebogamma 5% DIF. It is also not known whether Flebogamma 5% DIF can cause fetal harm when administered to a pregnant woman or can affect reproduction capacity. Immunoglobulins cross the placenta from maternal circulation increasingly after 30 weeks of gestation. Flebogamma 5% DIF should be given to a pregnant woman only if clearly needed.

8.2 Lactation

Risk Summary
There is no information regarding the presence of Flebogamma 5% DIF in human milk, its effects on the breastfed infant, or its effects on milk production. The developmental and health benefits of breastfeeding should be considered along with the mother’s clinical need for Flebogamma 5% DIF and any potential adverse effects on the breastfed infant from Flebogamma 5% DIF or from the underlying maternal condition.

8.4 Pediatric Use

Flebogamma 5% DIF was studied in a multicenter clinical trial for the treatment of PI in 24 subjects aged 2-16 years (seven were 2-5 years of age, seven were 6-11 years, and ten were 12-16 years), and found to be efficacious for the prevention of acute serious bacterial infections. No pediatric-specific dose requirements were necessary to achieve the desired serum IgG levels. Twenty subjects (83.3%) had at least one adverse reaction at some time during the study that was considered product-related. There were no deaths or serious adverse reactions. Treatment-related adverse reactions that occurred with an incidence of at least 5% on a per-subject basis included headache (42%), pyrexia (29%), hypotension (25%), tachycardia (25%), diastolic hypotension (21%), nausea (8%), abdominal pain (8%), diarrhea (8%), pain (8%), and vomiting (8%).

Safety and efficacy of Flebogamma 5% DIF in pediatric patients below the age of 2 years have not been established.

8.5 Geriatric Use

Limited information is available for the geriatric use of Flebogamma 5% DIF. Clinical studies of Flebogamma 5% DIF did not include sufficient numbers of subjects over the age of 65 to determine whether they respond differently from younger subjects. Use caution when administering Flebogamma 5% DIF to patients age 65 and over who are judged to be at increased risk for developing thrombosis or renal insufficiency. Do not exceed recommended dose, and administer Flebogamma 5% DIF at the minimum dose and infusion rate practicable, and at less than 0.06 mL per kg per minute (3 mg per kg per min). (see Boxed Warning, Warning and Precautions [5.2, 5.4], and Dosage and Administration [2.3])

10 OVERDOSAGE

Overdose may lead to fluid overload and hyperviscosity. Patients at particular risk of complications of fluid overload and hyperviscosity include elderly patients and patients with cardiac or renal impairment.

11 DESCRIPTION

Flebogamma 5% DIF is a ready to use, sterile, clear or slightly opalescent and colorless to pale yellow, liquid preparation of purified immunoglobulin (IgG) obtained from human plasma pools. The purification process includes cold ethanol fractionation, polyethylene glycol precipitation, ion exchange chromatography, low pH treatment, pasteurization, solvent detergent treatment, and Planova nanofiltration using 20 nanometer (nm) filters.

Flebogamma 5% DIF is a purified (at least 97% IgG), unmodified, human IgG. The distribution of the four IgG subclasses is approximately 66.6% IgG1, 28.5% IgG2, 2.7% IgG3, and 2.2% IgG4. Flebogamma 5% DIF contains trace amounts of IgA (typically less than 50 μg/mL) and trace amounts of sodium and IgM.

Flebogamma 5% DIF contains 5 g human normal immunoglobulin and 5 g D-sorbitol (as stabilizer) in 100 mL of water for injection, and ≤ 3 mg/mL polyethylene glycol. There is no preservative in the formulation. The pH of the solution ranges from 5 to 6 and the osmolality from 240 to 370 mOsm/kg, which is within the normal physiological range.

Screening against potentially infectious agents begins with the donor selection process and continues throughout plasma collections and plasma preparation. Each individual plasma donation used in the manufacture of Flebogamma 5% DIF is collected only at FDA-approved blood establishments and is tested by FDA-licensed serological test for hepatitis B virus (HBV) surface antigen (HBsAg), and for antibodies to human immunodeficiency virus (HIV-1/HIV-2) and hepatitis C virus (HCV) in accordance with U.S. regulatory requirements. As an additional safety measure, mini-pools of plasma are tested for the presence of HBV, HIV-1 and HCV by FDA-licensed nucleic acid testing (NAT) and found to be negative. In addition, plasma is tested by in-process NAT for hepatitis A virus (HAV) and parvovirus B19 (B19) on mini-pools and the viral load limit for B19 in the manufacturing pool is set not to exceed 10^4 IU/mL. NAT for the presence of HCV and HIV in the manufacturing plasma pool is also performed and found to be negative.

To further improve the margin of safety, three dedicated, independent virus inactivation/removal steps have been integrated into the manufacturing and formulation processes, namely pasteurization at 60 ºC, 10 hours, solvent-detergent treatment for 6 hours, and nanofiltration down to 20 nm Planova filters.

In vitro virus spiking studies have been used to validate the capability of the manufacturing process to inactivate and remove viruses. To establish the minimum applicable virus clearance capacity of the manufacturing process, these virus clearance studies were performed on seven steps of the production process (pasteurization, solvent-detergent treatment, nanofiltration, Fraction I precipitation, Fraction II+III precipitation, 4% PEG precipitation, and pH treatment for 4 hours at 37 ºC).

The viral reduction data (in log10) from these experiments are summarized in Table 2.

Table 2. Flebogamma 5% DIF: Viral Reduction Capacity of Combined Steps (log10)
Target virus | HIV-1, HIV-2 (env. RNA) | HBV Herpesvirus (env. DNA) |  | HCV (env. RNA) |  | WNV (env. RNA) | HAV (non-env. RNA) | Virus B19 (non-env. DNA)
Model virus | HIV-1 | PRV | IBR | BVDV | SINDBIS | WNV | EMC | PPV
Fraction I precipitation | < 1.00* | nd | nd | nd | nd | 2.78 | nd | < 1.00*
Ethanol incubation (Fraction II+III) | 1.48 | nd | nd | nd | nd | < 1.00* | nd | nd
PEG precipitation | ≥ 6.10 | ≥ 5.92 | nd | ≥ 5.78 | nd | nd | ≥ 6.41 | 6.35
Acid pH treatment | 2.47 | ≥ 5.32 | nd | < 1.00* | nd | nd | 1.36 | na
Pasteurization | ≥ 5.64 | ≥ 4.96 | ≥ 6.33 | ≥ 4.69 | ≥ 6.49 | ≥ 5.42 | ≥ 5.56 | 4.08
Solvent Detergent | ≥ 4.61 | ≥ 6.95 | nd | ≥ 6.14 | nd | ≥ 5.59 | na | na
Nanofiltration 20 nanometer | ≥ 4.81 | ≥ 4.63 | nd | ≥ 4.67 | nd | ≥ 3.63 | ≥ 5.92 | 4.61
Overall Reduction Capacity | ≥ 25.11 | ≥ 27.78 | ≥ 6.33 | ≥ 21.28 | ≥ 6.49 | ≥ 17.42 | ≥ 19.25 | 15.04
* When the RF is < 1 log10, it is not taken into account for the calculation of the overall reduction capacity.
≥ is no residual infectivity detected; nd = not done; na = non-applicable, since the virus is theoretically resistant to this treatment.
Abbreviations: HIV = Human immunodeficiency virus; PRV = Pseudorabies virus; IBR = Infectious bovine rhinotracheitis virus; BVDV = Bovine viral diarrhea virus; SINDBIS = Sindbis virus; WNV = West Nile virus; EMC = Encephalomyocarditis virus; PPV = Porcine parvovirus.

Additionally, the manufacturing process was investigated for its capacity to decrease infectivity of an experimental agent of transmissible spongiform encephalopathy (TSE), considered as a model for the vCJD and CJD agents. Several individual production steps in the Flebogamma 5% DIF manufacturing process have been shown to decrease TSE infectivity of an experimental model agent. TSE reduction steps include 4% polyethylene glycol precipitation [at least 6.19 log10] and Planova nanofiltration using a 20 nanometer filter [at least 5.45 log10]. These studies provide reasonable assurance that low levels of CJD/vCJD agent infectivity, if present in the starting material, would be removed.

12 CLINICAL PHARMACOLOGY

12.1 Mechanism of Action

Flebogamma 5% DIF, immune globulin intravenous (human), is a replacement therapy for PI. It supplies a broad spectrum of opsonizing and neutralizing IgG antibodies against a wide variety of bacterial and viral agents. Flebogamma 5% DIF also contains a spectrum of antibodies capable of reacting with cells such as erythrocytes. The role of these antibodies and the mechanisms of action of IgG in Flebogamma 5% DIF have not been fully elucidated.

12.3 Pharmacokinetics

In the clinical study assessing safety and efficacy in PI, Flebogamma 5% DIF was administered as an IV infusion (300-600 mg per kg) to subjects every 3 (n = 8) or 4 (n = 12) weeks for 12 months. The pharmacokinetics of total IgG was determined after the 7th infusion for the 3-week dosing interval and after the 5th infusion for the 4-week dosing interval (Table 3).

Table 3. Pharmacokinetic Variables of Total IgG in Subjects with PI
Variable | 3-Week Dosing Interval (n = 8) |  | 4-Week Dosing Interval (n = 12)
 | Mean [Range] | SD | Mean [Range] | SD
Cmax (mg/dL) | 1,929 [1,300-2,420] | 441 | 2,069 [1,590-2,800] | 338
AUC 0 - last (day·mg/dL) | 31,159 [20,458-40,104] | 6,572 | 32,894 [27,650-41,814] | 3,886
Clearance (mL/day) | 139 [81-243] | 57 | 109 [59-161] | 33
Half-life (days) a | 30 [19-41] | 9 | 32 [25-39] | 5
Trough IgG level (mg/dL) b | 951.38 [773.17-1143.15] | 132.42 | 899.89 [776.70-1,137.14] | 92.03
a. This half-life is an apparent value derived from a period of measurement of 28 days.
b. For subjects on the 3-week schedule, the average of the trough levels from Infusion 7 to the end of the study was calculated; for those on a 4-week schedule, the average of the trough levels from Infusion 5 to the end of the study was calculated. The means of the subject means are presented in this table.

There were 3 adolescent (up to 16 years of age) subjects who underwent pharmacokinetic testing, all of whom were on the 3-week infusion schedule. There were no clinically relevant differences among the adults and adolescents that were tested.

13 NONCLINICAL TOXICOLOGY

13.1 Carcinogenicity, Mutagenesis, Impairment of Fertility

No animal studies were conducted to evaluate the carcinogenic or mutagenic effect of Flebogamma 5% DIF or its effects on fertility.

13.2 Animal Toxicology and/or Pharmacology

Acute toxicity studies were performed in mice and rats at doses up to 2.5 g per kg body weight with infusion rates 6-37 times higher than the maximum rates recommended for humans. The most common clinical observations in mice studies were piloerection, ptosis, ataxia, and increase in respiration all lasting 90 minutes or less. No relevant adverse effects could be confirmed affecting respiratory, circulatory, renal, autonomic and central nervous systems, somatomotor activity, and behavior of the treated mice and rats.

Five of the 25 rats treated with the highest dose, approximately 8 times the maximum infusion rate recommended for humans, showed a transient “reddish urine” sign which was not confirmed as a relevant toxicity-causing phenomenon after renal macroscopic and microscopic analysis. This phenomenon was ascribed to hemolysis when serum was analyzed, suggesting a possible relation to cross reactivity of rodent red cells with human antibodies. No “reddish urine” was detected in any mouse, a much smaller animal where the rate of infusion was comparatively much higher than in rats. The macroscopic inspection of all treated mice did not show any renal alteration.

14 CLINICAL STUDIES

A multicenter, open-label, historically controlled study was conducted in the United States to assess the efficacy, safety, and pharmacokinetics of Flebogamma 5% DIF in adult and pediatric subjects with PI. A total of 46 subjects aged 15-75 years (63% male, 37% female) were enrolled and treated with Flebogamma 5% DIF at a dose of 300-600 mg per kg per infusion every 3-4 weeks for 12 months.

Since the subjects in the clinical study were assigned to two different treatment intervals (3-week vs. 4-week infusion schedules), the dosage had to be adjusted to ensure that the subjects received approximately the same dosage on an annualized basis. Therefore, subjects in the 3-week schedule received 75% of the monthly (4-week) dosage per infusion. This resulted in a mean annualized dosage of 451 mg per kg per month for subjects in the 3-week schedule (n=13, range 288-588 mg per kg per month) and 448 mg per kg per month for subjects in the 4-week schedule (n=33, range 298-591 mg per kg per month).

During the study period, the annual rate of acute serious bacterial infection, defined as bacterial pneumonia, bacteremia or sepsis, osteomyelitis/septic arthritis, visceral abscess, and bacterial meningitis per subject per year, was 0.021 (with an upper 1-sided 98% confidence interval of 0.112). One subject had one episode of bacterial pneumonia and there were no other episodes of serious bacterial infections reported (Table 4).

Table 4. Summary of Bacterial Infections (Intention-to-Treat Population, N = 46)
Infections | Subjects (N=46) N (%) | Episodes | Estimatesa | 98% CIb
Bacterial pneumonia | 1 (2.2) | 1
Bacteremia or sepsis | 0 (0.0) | 0
Osteomyelitis/septic arthritis | 0 (0.0) | 0
Bacterial meningitis | 0 (0.0) | 0
Total subjects | 1 (2.2) | 1 | 0.021 | (0.001-0.112)
a. Estimate = Total episodes/Total subject years.
b. The confidence interval is obtained by using a generalized linear model procedure for Poisson distribution.

The number of days of work/school missed, hospitalizations and days of each hospitalization, the number of visits to physicians or emergency rooms, other infections documented by positive radiographic findings and fever, and days on therapeutic and prophylactic oral/parenteral antibiotic use were also evaluated. These variables were annualized by using the subject-years exposure data of those subjects experiencing the events, but not the entire study cohort. With regard to the number of other validated infections, the mean rate was less than 2 days per subject per year (this calculation used all subjects, including those who had no infections). (Table 5)

Table 5. Summary of Annualized Efficacy Variables
Variable | Subjects |  | Mean number of events, days or visits per subject per yeara
 | N | %
Work/school days missed | 23 | 50.0 | 12.95
Days of normal activities missed | 18 | 39.1 | 7.28
Days in hospital | 4 | 8.7 | 0.77
Visits to physician/ER | 29 | 63.0 | 4.31
Number of other documented infectious episodes | 33 | 71.7 | 1.96
Days of therapeutic oral antibiotic use | 35 | 76.1 | 55.52
Days of therapeutic parenteral antibiotic use | 2 | 4.3 | 0.14
Days of other therapeutic antibiotic use | 16 | 34.8 | 44.30
Days of prophylactic oral antibiotic use | 19 | 41.3 | 81.08
Days of prophylactic parenteral antibiotic use | 1 | 2.3 | 0.02
Days of other prophylactic antibiotic use | 0 | 0.0 | 0.00
a. Days of work/school missed per subject year are derived as total days of work/school missed divided by total days in study multiplied by 365. If data are missing for a period (e.g. between Infusion 2 and Infusion 3), then number of days in this period is not counted in the denominator. All other endpoints are derived similarly.

A multicenter, open-label, historically controlled study was conducted in the United States to assess the efficacy of Flebogamma 5% DIF in pediatric subjects with PI. A total of 24 subjects aged 2-16 years (79% male, 21% female) were enrolled and treated with Flebogamma 5% DIF at a dose of 262-625 mg per kg per infusion every 3-4 weeks for 12 months.

The annual rate of acute serious bacterial infections, defined as bacterial pneumonia, bacteremia or sepsis, osteomyelitis/septic arthritis, visceral abscess, and bacterial meningitis per subject per year, was 0.051 (with an upper 1-sided 99% confidence limit of 0.53). One subject had one episode of bacterial pneumonia and there were no other episodes of serious bacterial infections reported.

15 REFERENCES

1. Cayco AV, Perazella MA, Hayslett JP. Renal insufficiency after intravenous immune globulin therapy: a report of two cases and an analysis of the literature. J Am Soc Nephrol 1997; 8:1788-94.
2. Winward DB, Brophy MT. Acute renal failure after administration of intravenous immunoglobulin: review of the literature and case report. Pharmacotherapy 1995; 15:765-72.
3. Tan E, Hajinazarian M, Bay W, et al. Acute renal failure resulting from intravenous immunoglobulin therapy. Arch Neurol 1993; 50:137-9.
4. Sekul EA, Cupler EJ, Dalakas MC. Aseptic meningitis associated with high-dose intravenous immunoglobulin therapy: frequency and risk factors. Ann Intern Med 1994; 121:259-62.
5. Kato E, Shindo S, Eto Y, et al. Administration of immune globulin associated with aseptic meningitis. JAMA 1988; 259:3269-71.
6. Casteels-Van Daele M, Wijndaele L, Hanninck K, et al. Intravenous immune globulin and acute aseptic meningitis. N Engl J Med 1990; 323:614-5.
7. Scribner CL, Kapit RM, Phillips ET, et al. Aseptic meningitis and intravenous immunoglobulin therapy. Ann Intern Med 1994; 121:305-6.
8. Copelan EA, Strohm PL, Kennedy MS, et al. Hemolysis following intravenous immune globulin therapy. Transfusion 1986; 26:410-2.
9. Thomas MJ, Misbah SA, Chapel HM, et al. Hemolysis after high-dose intravenous Ig. Blood 1993; 15:3789.
10. Reinhart WH, Berchtold PE. Effect of high-dose intravenous immunoglobulin therapy on blood rheology. Lancet 1992; 339:662-4.
11. Wilson JR, Bhoopalam N, Fisher M. Hemolytic anemia associated with intravenous immunoglobulin. Muscle Nerve 1997; 20:1142-1145.
12. Kessary-Shoham H, Levy Y, Shoenfeld Y, et al. In vivo administration of intravenous immunoglobulin (IVIG) can lead to enhanced erythrocyte sequestration. J Autoimmune 1999; 13:129-35.
13. Kahwaji J, Barker E, Pepkowitz S, et al. Acute hemolysis after high-dose intravenous immunoglobulin therapy in highly HLA sensitized patients. Clin J Am Soc Nephrol 2009; 4:1993-1997.
14. Daw Z, Padmore R, Neurath D, et al. Hemolytic transfusion reactions after administration of intravenous immune (gamma) globulin: A case series analysis. Transfusion 2008; 48:1598-1601.
15. Rizk A, Gorson KC, Kenney L, et al. Transfusion-related acute lung injury after the infusion of IVIG. Transfusion 2001; 41:264-8.
16. Pierce LR, Jain N. Risks associated with the use of intravenous immunoglobulin. Transfus Med Rev 2003; 17:241-51.
17. Orbach H, Katz U, Sherer Y, Shoenfeld Y. Intravenous immunoglobulin: adverse effects and safe administration. Clin Rev Allergy Immunol, 2005; 29:173-184.

16 HOW SUPPLIED/STORAGE AND HANDLING

Flebogamma 5% DIF is supplied in single-use, individually laser-etched vials containing the labeled amount of functionally active IgG. The following presentations of Flebogamma 5% DIF are available:

NDC Number | Size | Grams Protein
61953-0004-1 | 10 mL | 0.5 g
61953-0004-2 | 50 mL | 2.5 g
61953-0004-3 | 100 mL | 5.0 g
61953-0004-4 | 200 mL | 10.0 g
61953-0004-5 | 400 mL | 20.0 g

Each vial has an integral suspension band and a label with two peel-off strips showing the product name and lot number.

Flebogamma 5% DIF may be stored at room temperature at 2 to 25 ºC (36 to 77 ºF) for 24 months, as indicated by the expiration date printed on the outer carton and container label. Discard after expiration date. Do not freeze.

Keep Flebogamma 5% DIF in its original carton to protect it from light.

Not made with natural rubber latex.

17 PATIENT COUNSELING INFORMATION

Instruct patients to immediately report the following signs and symptoms to their physician:

- Decreased urine output, sudden weight gain, fluid retention/edema, and/or shortness of breath (see Renal Failure [5.2])
- Symptoms of thrombosis which may include: pain and/or swelling of an arm or leg with warmth over the affected area, discoloration of an arm or leg, unexplained shortness of breath, chest pain or discomfort that worsens on deep breathing, unexplained rapid pulse, numbness or weakness on one side of the body (see Thrombosis [5.4])
- Severe headache, neck stiffness, drowsiness, fever, sensitivity to light, painful eye movements, nausea, and vomiting (see Aseptic Meningitis Syndrome [5.5])
- Fatigue, increased heart rate, yellowing of the skin or eyes, and dark-colored urine (see Hemolysis [5.6])
- Trouble breathing, chest pain, blue lips or extremities, fever (see TRALI [5.7])

Inform patients that Flebogamma 5% DIF is made from human plasma and may contain infectious agents that can cause disease (e.g., viruses, the vCJD agent and, theoretically, the CJD agent). The risk of Flebogamma 5% DIF transmitting an infectious agent has been reduced by screening plasma donors for prior exposure, testing the donated plasma, and inactivating and/or removing certain viruses during manufacturing. (see Warnings and Precautions [5.8]) Instruct patients to report any symptoms that concern them and might be caused by infections.

Inform patients that Flebogamma 5% DIF may interfere with their immune response to live viral vaccines such as measles, mumps, and rubella. Inform patients to notify their health care professional of this potential interaction when they are receiving vaccinations. (see Drug Interactions [7])

Manufactured by:
INSTITUTO GRIFOLS, S.A.
BARCELONA – SPAIN
U.S. License No. 1181

Principal Display Panel - Vial Label

NDC 61953-0004-8 5 g in 100 mL
Immune Globulin
Intravenous (Human)
Flebogamma® 5% DIF
5%
GRIFOLS Rx only
Dosage and directions for administration,
see package insert.
Store at 2 - 25 °C (36 - 77 °F).
DO NOT USE IF TURBID.
ONCE THE CONTAINER HAS BEEN
ENTERED IT SHOULD BE USED
PROMPTLY.
Manufactured by
Instituto Grifols, S. A.
Barcelona - SPAIN
U.S. License No. 1181
3065988
Lot No.:
Expires:

Principal Display Panel - Carton Label

NDC 61953-0004-3 5 g in 100 mL
Immune Globulin
Intravenous (Human)
Flebogamma® 5% DIF
Solution for infusion
5%
Nanofiltered (20 nm)
Store at 2 - 25 °C (36 - 77 °F)
GRIFOLS
Contents
One each: 100 mL vial Immune Globulin
Intravenous (Human)
Each 100 mL contains 5 g Immune
Globulin (Human),
5 g D-sorbitol
Protein content is 50 g/L
Contains no preservatives.
The patient and physician should discuss
the risks and benefits of this product.
Instructions
For information on dosage and directions
for administration, see enclosed package
insert.
Manufactured by
Instituto Grifols, S.A.
Barcelona - SPAIN
U.S. License No. 1181
Rx only
Precaution
Do not allow to freeze.
Single dose container for intravenous
administration.
Discard any unused contents and
administration devices after use.
DO NOT USE IF TURBID.
ONCE THE CONTAINER HAS BEEN
ENTERED IT SHOULD BE USED
PROMPTLY.
GTIN: 00361953000432
SN: XXXXXXXXXXXXXXXX
Lot: XXXXXXXXXX
Exp.: DD-MMM-YY
3065994

Principal Display Panel - Vial Label

NDC 61953-0004-9 10 g in 200 mL
Immune Globulin
Intravenous (Human)
Flebogamma® 5% DIF
5%
GRIFOLS Rx only
CONTENTS: Each 200 mL contains
Immune Globulin (Human) 10 g; D-sorbitol 10 g;
Protein content is 50 g/L
Dosage and directions for administration, see
package insert.
Store at 2 - 25 °C (36 - 77 °F).
DO NOT USE IF TURBID. ONCE THE CONTAINER HAS
BEEN ENTERED IT SHOULD BE USED PROMPTLY.
The patient and physician should discuss the risks
and benefits of this product.
Manufactured by Instituto Grifols, S. A.
Barcelona - SPAIN U.S. License No. 1181
3065987
Lot No.:
Expires:

Principal Display Panel - Carton Label

NDC 61953-0004-4 10 g in 200 mL
Immune Globulin
Intravenous (Human)
Flebogamma® 5% DIF
Solution for infusion
5%
Nanofiltered (20 nm)
Store at 2 - 25 °C (36 - 77 °F)
GRIFOLS
Contents
One each: 200 mL vial Immune Globulin
Intravenous (Human)
Each 200 mL contains 10 g Immune Globulin
(Human),
10 g D-sorbitol
Protein content is 50 g/L
Contains no preservatives.
The patient and physician should discuss the
risks and benefits of this product.
Instructions
For information on dosage and directions for
administration, see enclosed package insert.
Manufactured by
Instituto Grifols, S.A.
Barcelona - SPAIN
U.S. License No. 1181
Rx only
Precaution
Do not allow to freeze.
Single dose container for intravenous
administration.
Discard any unused contents and
administration devices after use.
DO NOT USE IF TURBID.
ONCE THE CONTAINER HAS BEEN
ENTERED IT SHOULD BE USED
PROMPTLY.
GTIN: 00361953000449
SN: XXXXXXXXXXXXXXXX
Lot: XXXXXXXXXX
Exp.: DD-MMM-YY
3065993

Principal Display Panel - Vial Label

NDC 61953-0004-0 20 g in 400 mL
Immune Globulin
Intravenous (Human)
Flebogamma® 5% DIF
5%
GRIFOLS Rx only
CONTENTS: Each 400 mL contains Immune Globulin (Human)
20 g; D-sorbitol 20 g; Protein content is 50 g/L
Dosage and directions for administration, see package insert.
Store at 2 - 25 °C (36 - 77 °F).
DO NOT USE IF TURBID. ONCE THE CONTAINER HAS BEEN
ENTERED IT SHOULD BE USED PROMPTLY.
The patient and physician should discuss the risks and
benefits of this product.
Manufactured by Instituto Grifols, S. A.
Barcelona - SPAIN
U.S. License No. 1181
3065986
Lot No.:
Expires:

Principal Display Panel - Carton Label

NDC 61953-0004-5 20 g in 400 mL
Immune Globulin
Intravenous (Human)
Flebogamma® 5% DIF
Solution for infusion
5%
Nanofiltered (20 nm)
Store at 2 - 25 °C (36 - 77 °F)
GRIFOLS
Contents
One each: 400 mL vial Immune Globulin
Intravenous (Human)
Each 400 mL contains 20 g Immune Globulin
(Human),
20 g D-sorbitol
Protein content is 50 g/L
Contains no preservatives.
The patient and physician should discuss the
risks and benefits of this product.
Instructions
For information on dosage and directions for
administration, see enclosed package insert.
Manufactured by
Instituto Grifols, S.A.
Barcelona - SPAIN
U.S. License No. 1181
Rx only
Precaution
Do not allow to freeze.
Single dose container for intravenous
administration.
Discard any unused contents and
administration devices after use.
DO NOT USE IF TURBID.
ONCE THE CONTAINER HAS BEEN ENTERED
IT SHOULD BE USED PROMPTLY.
GTIN: 00361953000456
SN: XXXXXXXXXXXXXXXX
Lot: XXXXXXXXXX
Exp.: DD-MMM-YY
3065992